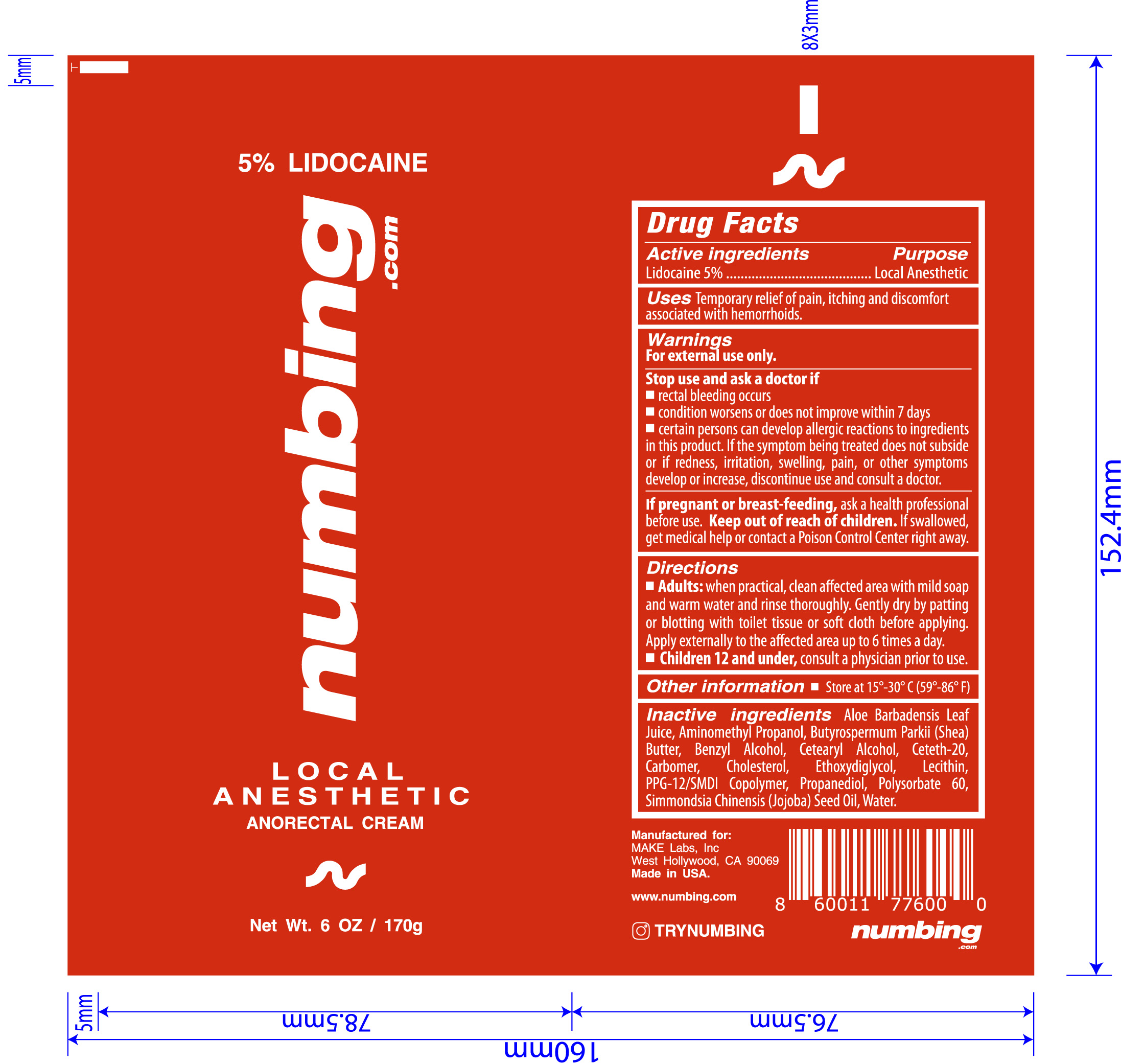 DRUG LABEL: Local Anesthetic Anorectal Cream
NDC: 84767-001 | Form: CREAM
Manufacturer: Make Labs LLC
Category: otc | Type: HUMAN OTC DRUG LABEL
Date: 20240918

ACTIVE INGREDIENTS: LIDOCAINE 5 g/100 g
INACTIVE INGREDIENTS: ALOE VERA LEAF; SHEA BUTTER; CHOLESTEROL; LECITHIN, SUNFLOWER; AMINOMETHYLPROPANOL; BENZYL ALCOHOL; CETOSTEARYL ALCOHOL; CETETH-20; CARBOMER HOMOPOLYMER, UNSPECIFIED TYPE; DIETHYLENE GLYCOL MONOETHYL ETHER; PPG-12/SMDI COPOLYMER; PROPANEDIOL; POLYSORBATE 60; JOJOBA OIL; WATER

Local Anesthetic Anorectal Cream

Active Ingredients purpose

Lidocaine 5%........Local Anesthetic

Uses

Temporary relief of pain, itching, and discomfort associated with hemorrhoids

Keep out of reach of children. If swallowed, get medical help or contact a Poison Control Center right away.

Stop use and ask a doctor if

- rectal bleeding occurs
- condition worsens or does not improve within 7 days
- certain persons can develop allergic reactions to ingredients in this product. If the symptom being treated does not subside or if redness, irritation, swelling, pain, or other symptoms develop or increase, discontinue use and consult a doctor.

Warnings

For external use only

If pregnant or breast-feeding, ask a health professional before use.

Directions

- Adults: When practical, clean affected area with mild soap and warm water and rinse thoroughly. Gently dry by patting or blotting with toilet tissue or soft cloth before applying. Apply externally to the affected area up to 6 times a day.
- Children 12 and under, consult a physician prior to use.

INACTIVE INGREDIENT

Inactive ingredients Aloe Barbadensis Leaf Juice, Aminomethyl Propanol, Butyrospermum Parkii (Shea) Butter, Benzyl Alcohol, Cetearyl Alcohol, Ceteth-20, Carbomer, Cholesterol, Ethoxydiglycol, Lecithin, PPG-12/SMDI Copolymer, Propanediol, Polysorbate 60, Simmondsia Chinensis (Jojoba) Seed Oil, Water.

PACKAGE LABEL

numbing.com

Local Anesthetic

Anorectal Cream

Net Wt. 6 OZ / 170g